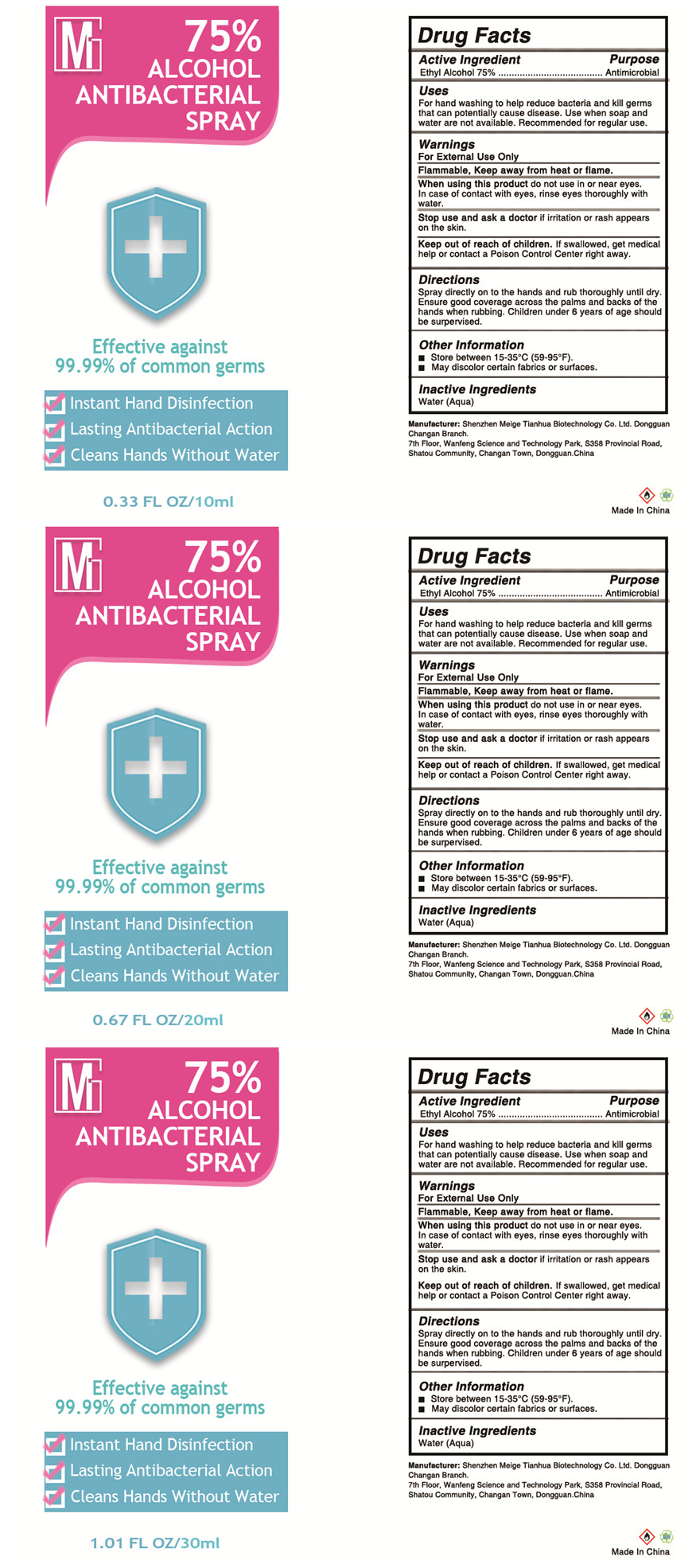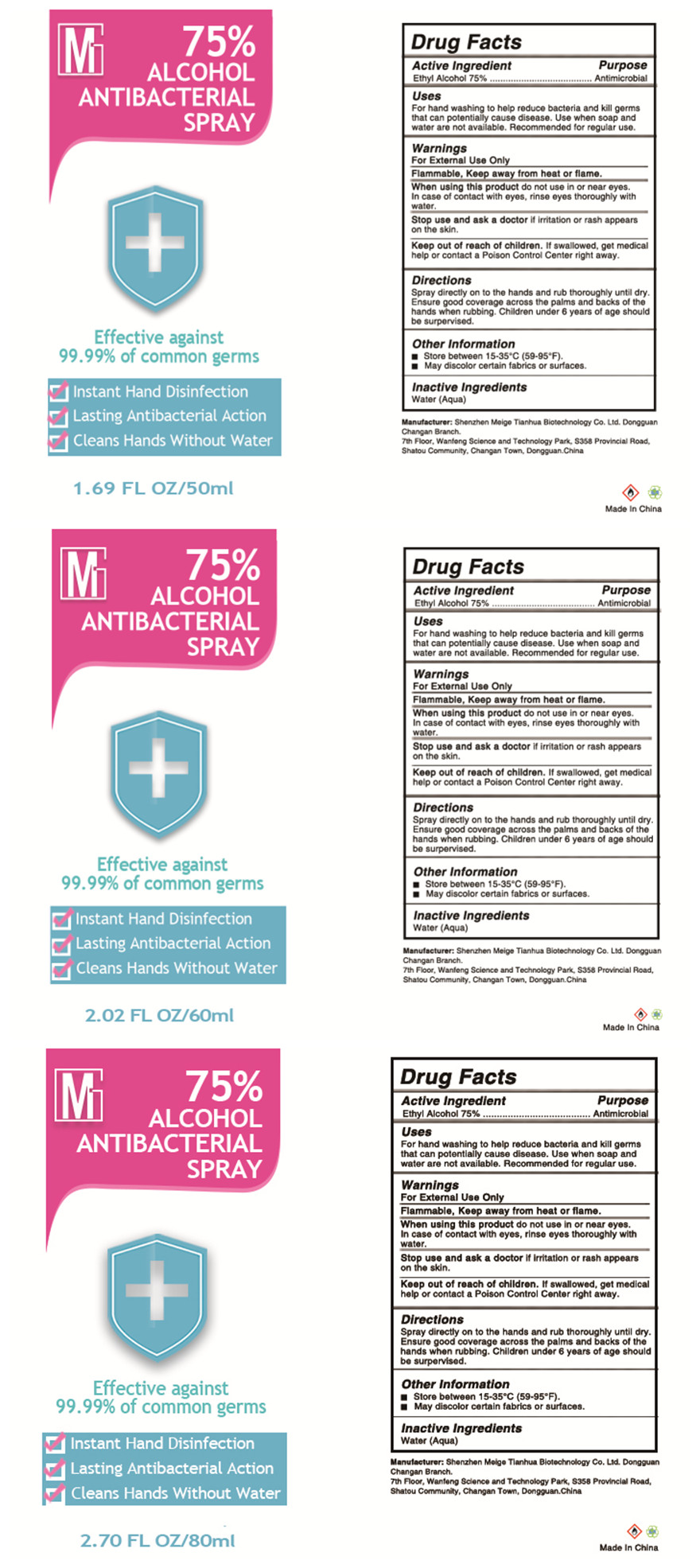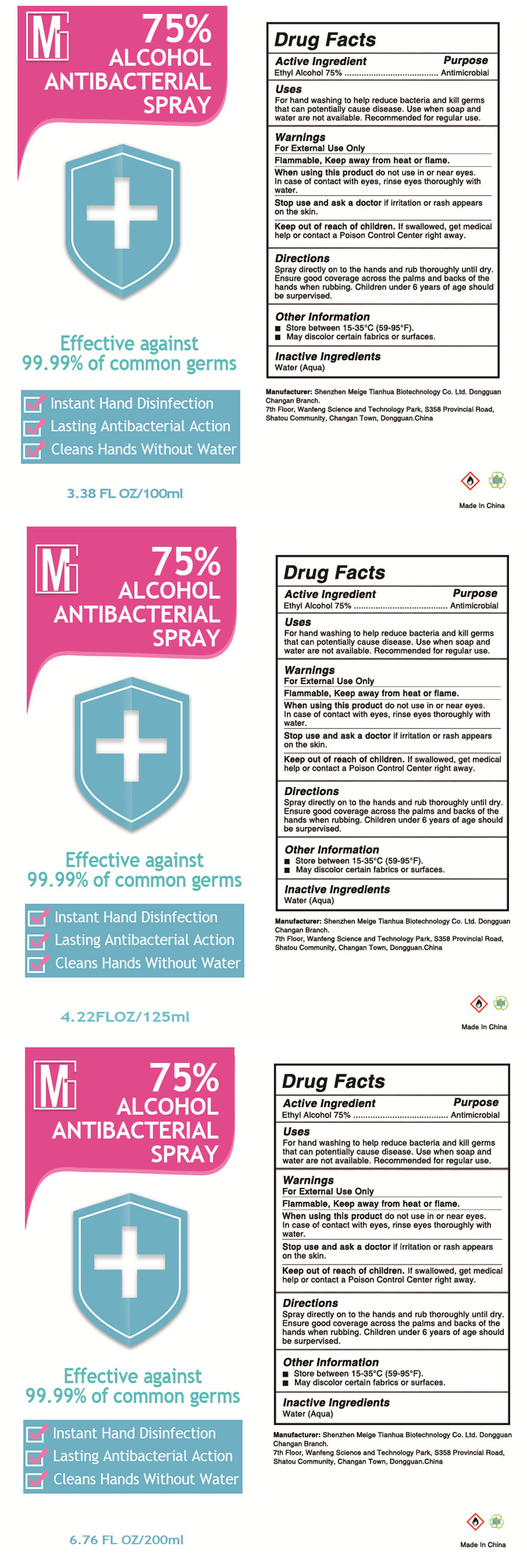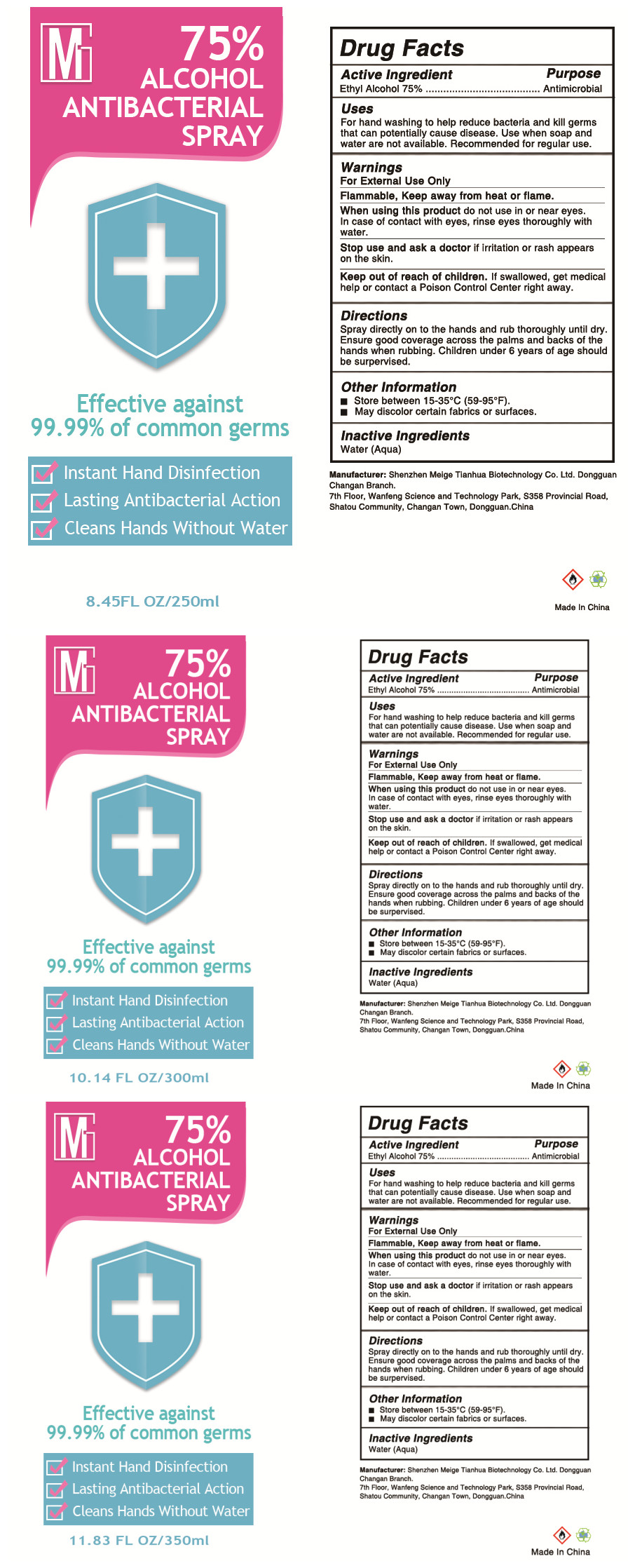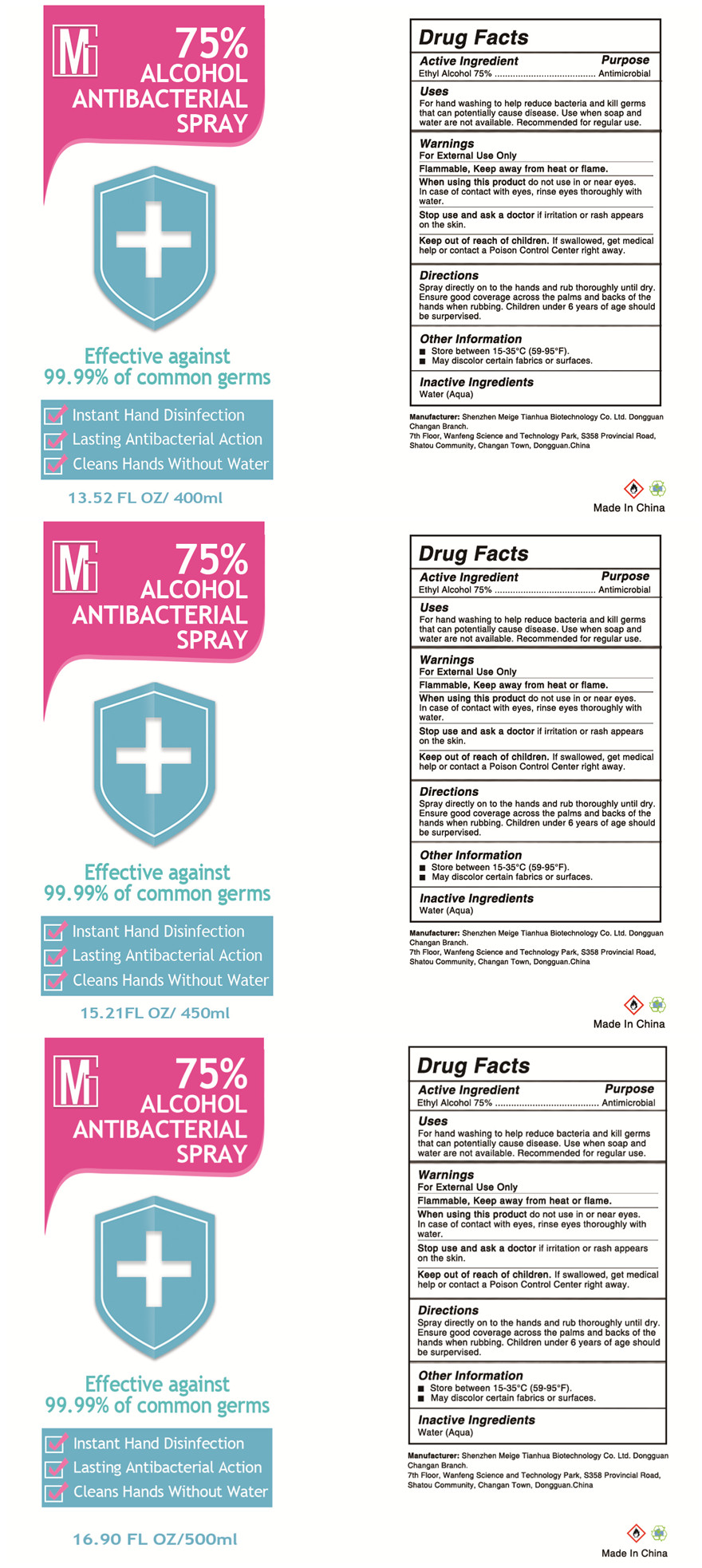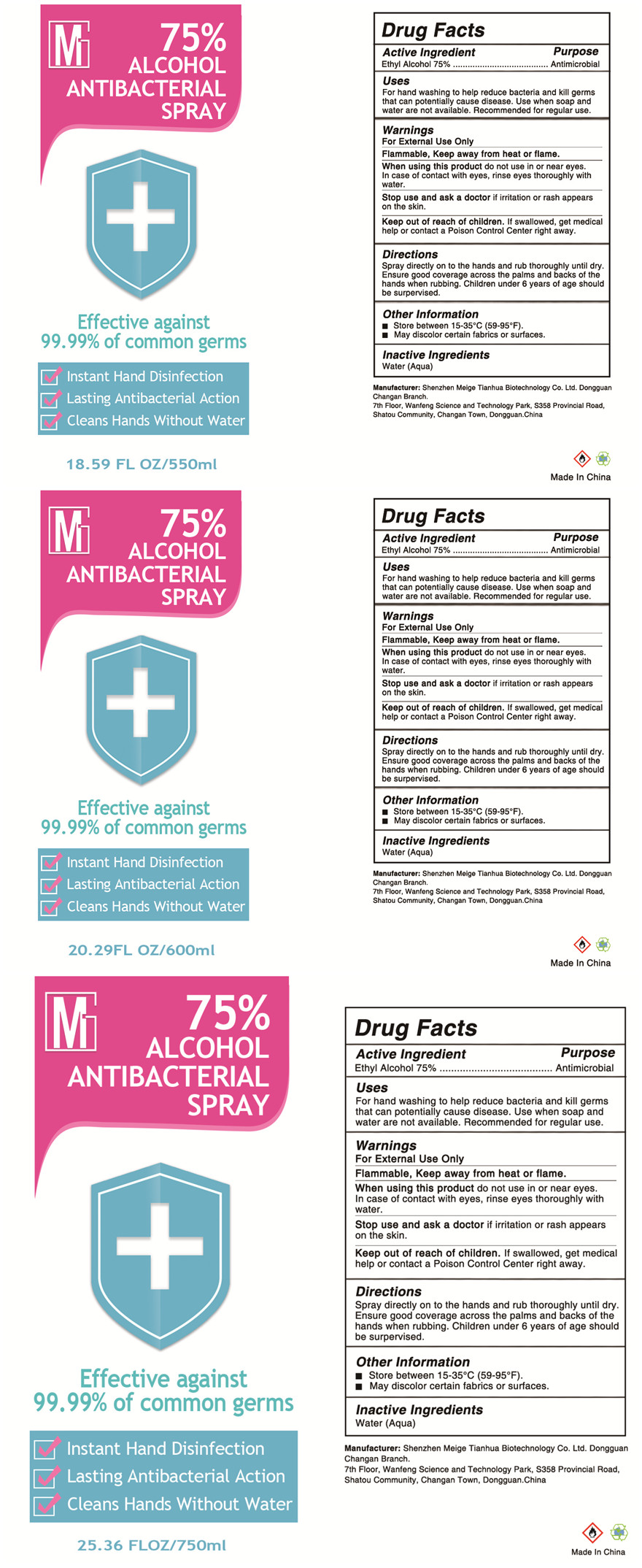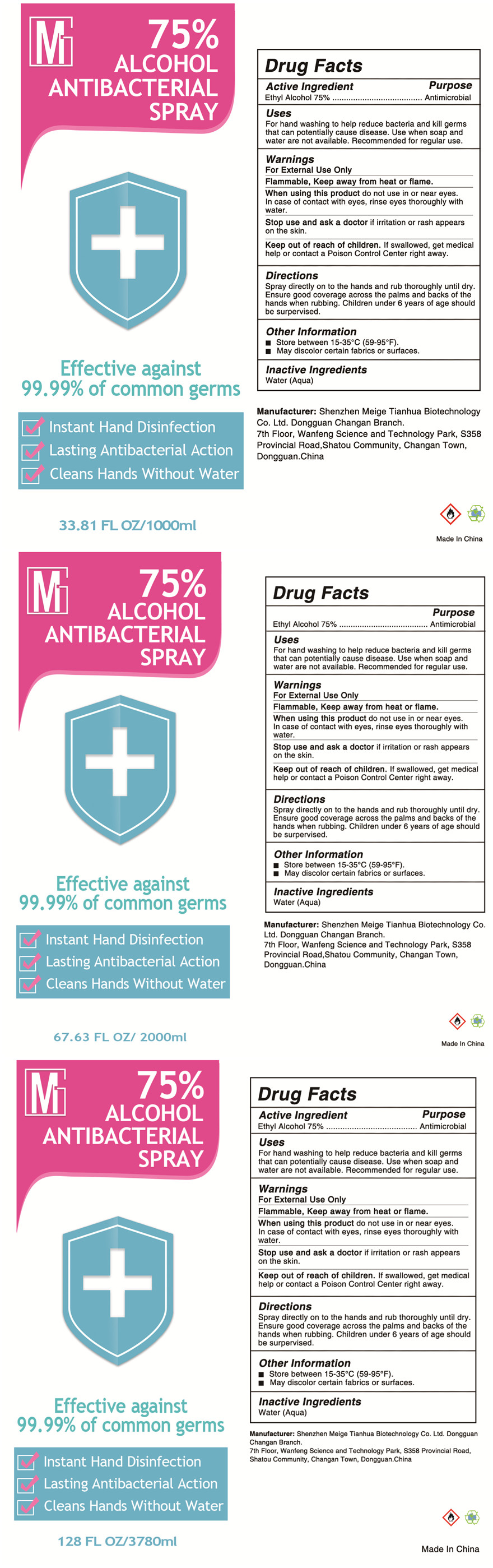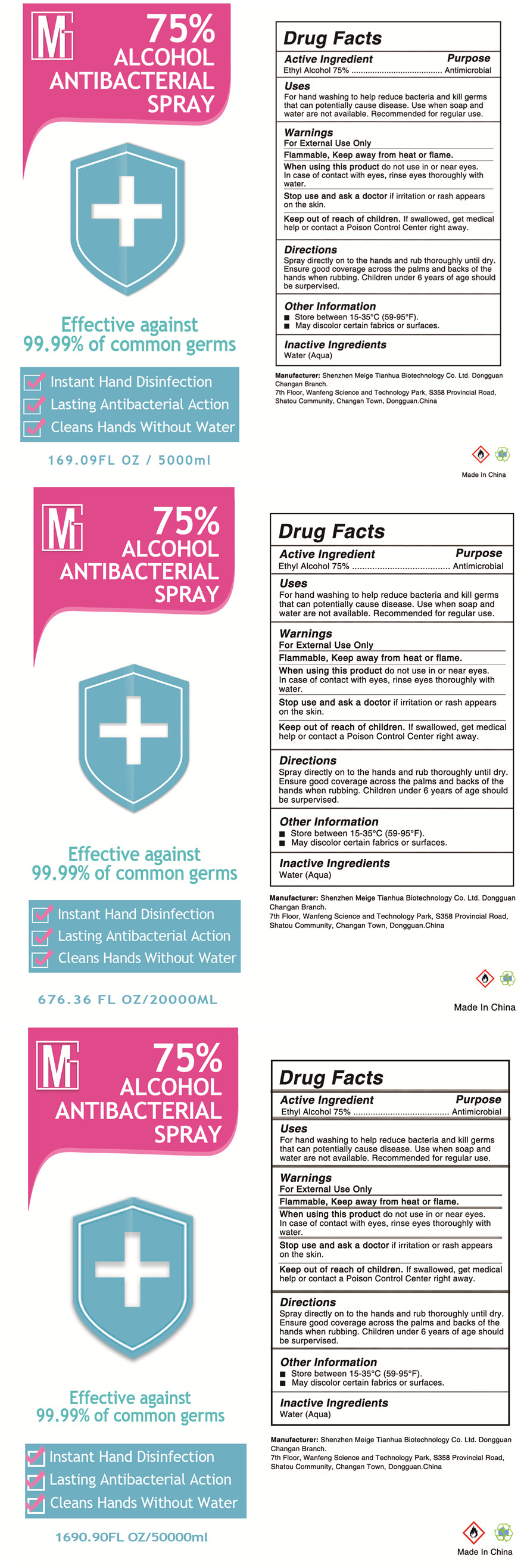 DRUG LABEL: 75% ALCOHOL ANTIBACTERIAL
NDC: 74272-004 | Form: SPRAY
Manufacturer: Shenzhen Meige Tianhua Biological Technology Co., Ltd. Dongguan Changan Branch
Category: otc | Type: HUMAN OTC DRUG LABEL
Date: 20200629

ACTIVE INGREDIENTS: ALCOHOL 75 mL/100 mL
INACTIVE INGREDIENTS: WATER

75% ALCOHOL ANTIBACTERIAL SPRAY

Active Ingredient

Ethyl Alcohol 75%.

Purpose

Antimicrobial

Uses

For hand washing to help reduce bacteria and kill germs that can potentially cause disease.Use when soap and

water are not available.Recommended for regular use.

Warnings

For External Use Only

Flammable,Keep away from heat or flame.

When using this product

do not use in or near eyes.

In case of contact with eyes, rinse eyes thoroughly with water.

Stop use and ask a doctor

if irritation or rash appears on the skin.

Keep out of reach of children

If swallowed, get medical help or contact a Poison Control Center right away.

Directions

Spray directly on to the hands and rub thoroughly until dry.Ensure good coverage across the palms and backs of the

hands when rubbing.Children under 6 years of age should be surpervised.

Other Information

Store between 15-35°C(59-95°F) .

May discolor certain fabrics or surfaces.

Inactive Ingredients

Water(Aqua)